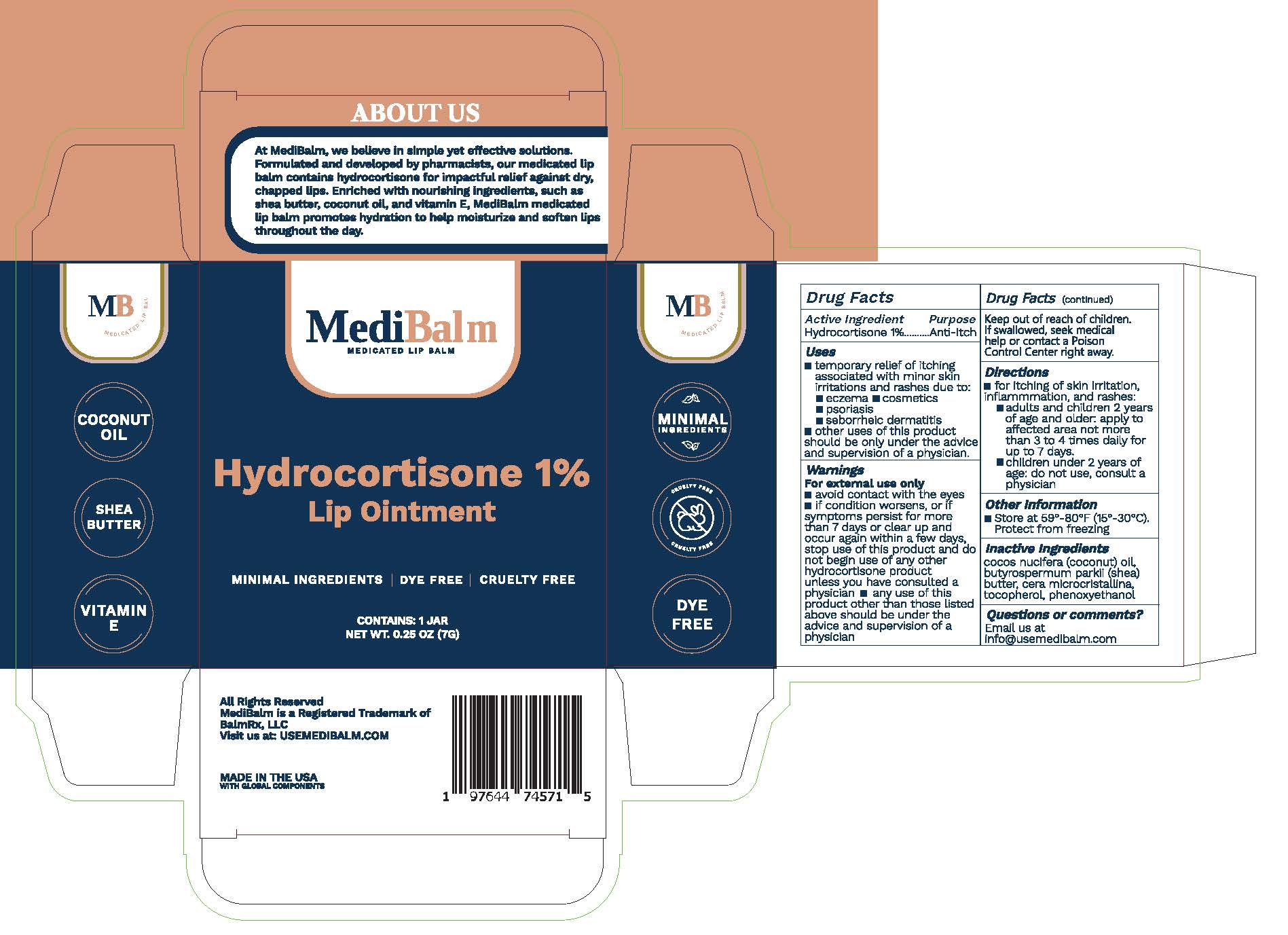 DRUG LABEL: MediBalm
NDC: 85529-204 | Form: OINTMENT
Manufacturer: BalmRx, LLC
Category: otc | Type: HUMAN OTC DRUG LABEL
Date: 20250626

ACTIVE INGREDIENTS: HYDROCORTISONE 1 g/100 g
INACTIVE INGREDIENTS: MICROCRYSTALLINE WAX; PHENOXYETHANOL; TOCOPHEROL; COCOS NUCIFERA (COCONUT) OIL; BUTYROSPERMUM PARKII (SHEA) BUTTER

ACTIVE INGREDIENT PURPOSE
Hydrocortisone 1.0%...........Anti-Itch

ACTIVE INGREDIENT PURPOSE
Hydrocortisone 1.0%...........Anti-Itch

USES

For the temporary relief of itching
associated with minor skin
irritations and rashes due to:

- Eczema
- Cosmetics
- Psoriasis
- Seborrheic Dermatitis
- Other uses of this product should

be only under the advice and
supervision of a physician.

WARNINGS

For external use only. Avoid contact with eyes.

STOP USE

and ask a doctor if condition worsens, or if symptoms persist for more than 7 days or clear up and occur again within a few days. Any use of this product other than those listed above should be under the advice and supervision of a doctor.

DO NOT USE

for the treatment of diaper rash. Consult a doctor.

Keep out of reach of children

DOSAGE AND ADMINISTRATION

D IRECTIONS

- Adults and children 2 years of

age and older: apply to affected
area not more than 3 to 4 times
daily for up to 7 days.

- Children under 2 years of age:

do not use, consult a physician

INACTIVE INGREDIENTS

coconut oil, shea butter, cera
microcristallina, tocopherol,
phenoxyethanol

OTHER INFORMATION

Store at 59-80 F (15-30 C).
Protect from freezing.

RECENT MAJOR CHANGES

- Removed "Warnings and Precautions section"
- Added "OTC - Purpose section" - "ACTIVE INGREDIENT PURPOSE Hydrocortisone 1.0%...........Anti-Itch"
- Added "Warnings section" - "For external use only. Avoid contact with eyes."
- Added "OTC - Stop use section" - "and ask a doctor if condition worsens, or if symptoms persist for more than 7 days or clear up and occur again within a few days. Any use of this product other than those listed above should be under the advice and supervision of a doctor."
- Added "OTC - Do not use section" - "for the treatment of diaper rash. Consult a doctor."
- Added "OTC - Keep out of reach of Children section"